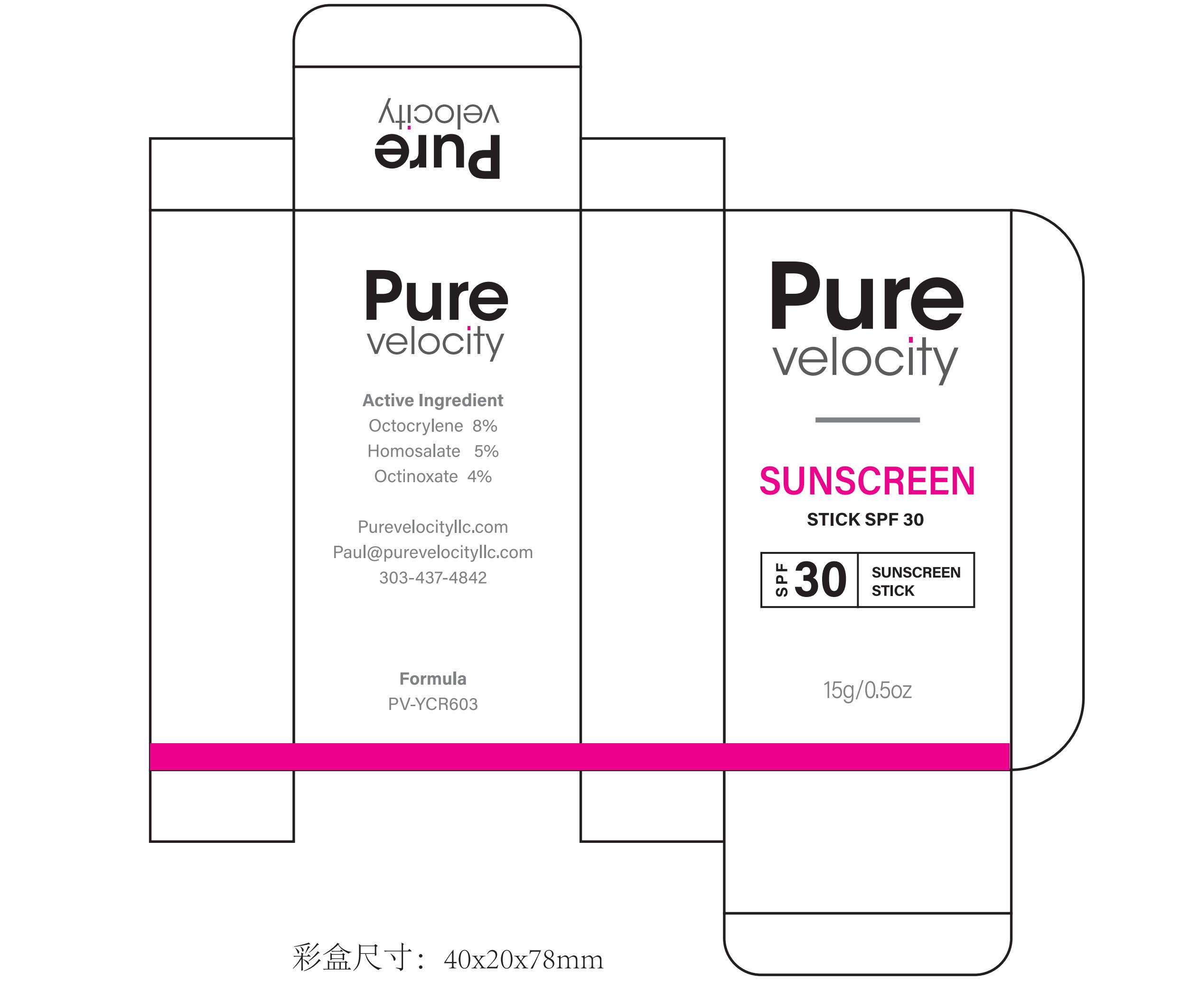 DRUG LABEL: Pure Velocity SUNSCREEN SPF30
NDC: 60771-0030 | Form: STICK
Manufacturer: Guangzhou Haishi Biological Technology Co., Ltd.
Category: otc | Type: HUMAN OTC DRUG LABEL
Date: 20250930

ACTIVE INGREDIENTS: ETHYLHEXYL METHOXYCINNAMATE 2 g/100 g; HOMOSALATE 2.5 g/100 g; OCTOCRYLENE 4 g/100 g
INACTIVE INGREDIENTS: CYCLOPENTASILOXANE; MICROCRYSTALLINE WAX; DICAPRYLYL CARBONATE; POLYMETHYLSILSESQUIOXANE (11 MICRONS); PHENOXYETHANOL; ETHYLHEXYL PALMITATE; POLYGLYCERYL-2 TRIISOSTEARATE; PARFUMIDINE; BEESWAX; CERAMIDE NP; CYCLOHEXASILOXANE; SILICON DIOXIDE; TOCOPHEROL; BISABOLOL; THEOBROMA CACAO (COCOA) SEED BUTTER

Active Ingredients

OCTOCRYLENE 4%
HOMOSALATE 2.5%
ETHYLHEXYL METHOXYCINNAMATE 2%

Purpose

SUNSCREEN

Uses

If used as directed with other sun protection measures(see Directions)，decreases the risk of skin cancer and early skin aging caused by the sun.

Warnings

For external use only

Stop Use

Rinse with wate to remove.
Stop use and ask doctor if rash occurs.

Do not use on damaged or broken skin.

When Using

When using this product keep out of eyes.

Keep Out Of Reach Of Children

Dosage & administration

Squeeze out an appropriate amount of Sunscreen and spread evenly on skin.

Inactive ingredients

CYCLOPENTASILOXANE 15%

CYCLOHEXASILOXANE 7.5%

ETHYLHEXYL PALMITATE 6%

OZOKERITE 2.5%

MICROCRYSTALLINE WAX 2.5%

DICAPRYLYL CARBONATE 3%

THEOBROMA CACAO (COCOA) SEED BUTTER 2%

SILICA 1%

POLYMETHYLSILSESQUIOXANE 3%

CERAMIDE NP 0.5%

POLYGLYCERYL-2 TRIISOSTEARATE 1%

BISABOLOL 0.1%

TOCOPHEROL 0.2%

PHENOXYETHANOL 0.35%

AROMA 0.3%